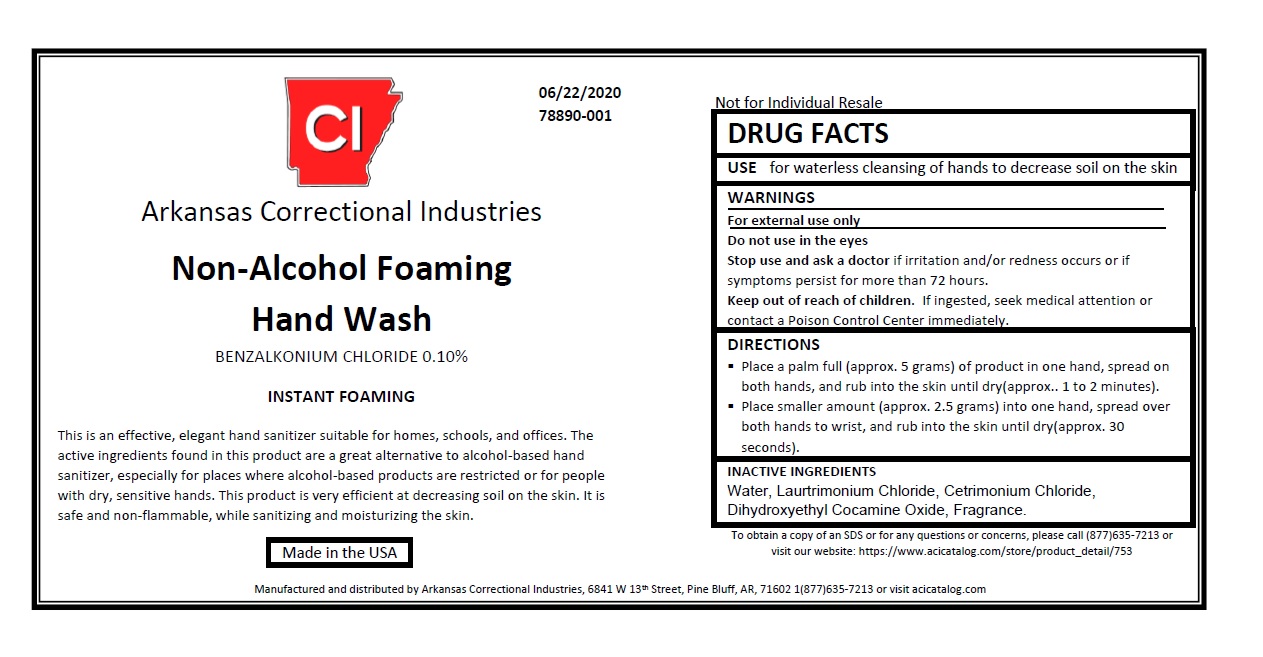 DRUG LABEL: Non-Alcohol Foaming Hand Wash
NDC: 78890-001 | Form: LIQUID
Manufacturer: Arkansas Correctional Industries
Category: otc | Type: HUMAN OTC DRUG LABEL
Date: 20231004

ACTIVE INGREDIENTS: BENZALKONIUM CHLORIDE 0.1 g/100 mL
INACTIVE INGREDIENTS: CETRIMONIUM CHLORIDE 0.01 g/100 mL; DIHYDROXYETHYL COCAMINE OXIDE 0.01 g/100 mL; WATER 99.87 g/100 mL; LAURTRIMONIUM CHLORIDE 0.01 g/100 mL

Non-Alcohol Foaming Hand Sanitizing Wash

Active Ingredients

[See: INNERMOST LABEL.jpg] [See: OUTERMOST LABEL.jpg] BENZALKONIUM CHLORIDE 0.10%

Do not use in the eyes

Stop use and ask a doctor if irritation and/or redness occurs or if symptoms persist for more than 72 hours.

Keep out of reach of children. If ingested, seek medical attention or contact a Poison Control Center immediately.

PURPOSE

USE for waterless cleansing of hands to decrease soil on the skin

QUESTIONS

To obtain a copy of an SDS or for any questions or concerns, please call (877)635-7213 or visit our website: https://www.acicatalog.com/store/product_detail/753

WARNINGS

For external use only

Do not use in the eyes

Stop use and ask a doctor if irritation and/or redness occurs or if symptoms persist for more than 72 hours.

Keep out of reach of children. If ingested, seek medical attention or contact a Poison Control Center immediately.

INACTIVE INGREDIENTS

Water, Laurtrimonium Chloride, Cetrimonium Chloride, Dihydroxyethyl Cocamine Oxide, Fragrance.

DIRECTIONS

Place a palm full (approx. 5 grams) of product in one hand, spread on both hands, and rub into the skin until dry(approximately 1 to 2 minutes).
Place smaller amount (approx. 2.5 grams) into one hand, spread over both hands to wrist, and rub into the skin until dry(approximately 30 seconds).

INDICATIONS AND USAGE

USE for waterless cleansing of hands to decrease soil on the skin